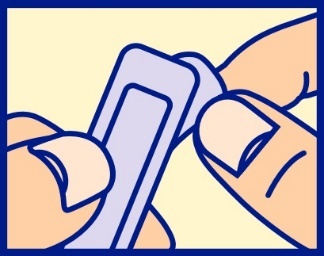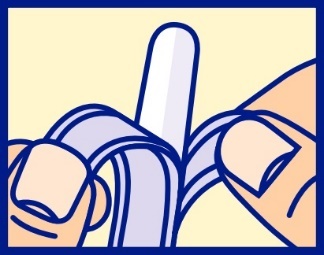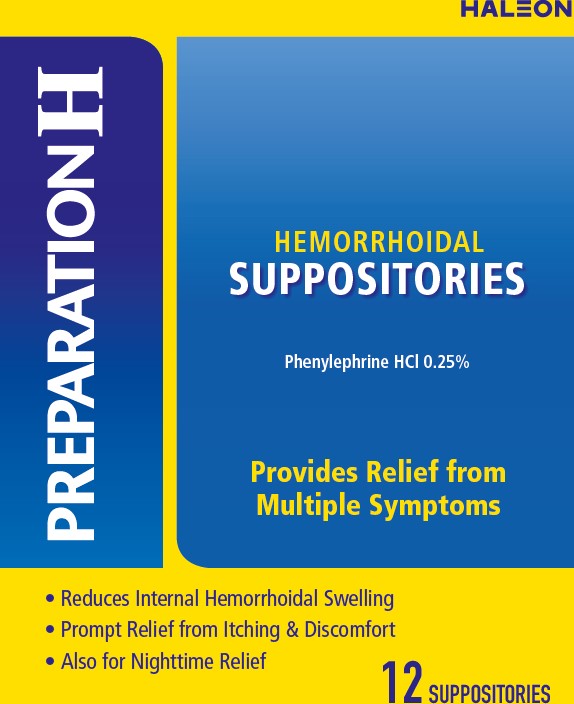 DRUG LABEL: PREPARATION H
NDC: 0573-2919 | Form: SUPPOSITORY
Manufacturer: Haleon US Holdings LLC
Category: otc | Type: HUMAN OTC DRUG LABEL
Date: 20251218

ACTIVE INGREDIENTS: PHENYLEPHRINE HYDROCHLORIDE 6.25 mg/1 1
INACTIVE INGREDIENTS: COCOA BUTTER; STARCH, CORN; METHYLPARABEN; PROPYLPARABEN

Drug Facts

Active ingredient (in each suppository)

Phenylephrine HCl 0.25%

Purpose

Vasoconstrictor

Uses

- helps relieve the local itching and discomfort associated with hemorrhoids
- temporarily shrinks hemorrhoidal tissue
- temporarily reduces the swelling associated with irritation in hemorrhoids and other anorectal disorders

Warnings

For rectal use only

Ask a doctor before use if you have

- heart disease
- high blood pressure
- thyroid disease
- diabetes
- difficulty in urination due to enlargement of the prostate gland

Ask a doctor or pharmacist before use if you are

- presently taking a prescription drug for high blood pressure or depression

When using this product

do not exceed the recommended daily dosage unless directed by a doctor.

Stop use and ask a doctor if

- bleeding occurs
- condition worsens or does not improve within 7 days

If pregnant or breast feeding

ask a health professional before use.

Keep out of reach of children

If swallowed, get medical help or contact a Poison Control Center right away.

Directions

- adults: when practical, cleanse the affected area by patting or blotting with an appropriate cleansing wipe. Gently dry by patting or blotting with a tissue or a soft cloth before insertion of this product.
- detach one suppository from the strip; remove the foil wrapper before inserting into the rectum as follows:
  - hold suppository with the rounded end up
  - as shown, carefully separate foil tabs by inserting tip of fingernail at end marked “peel down”
  - slowly and evenly peel apart (do not tear) foil by pulling tabs down both sides, to expose the suppository
  - remove exposed suppository from the wrapper
  - insert one suppository into the rectum up to 4 times daily, especially at night, in the morning or after each bowel movement
- children under 12 years of age: consult a doctor

Other information

- store at 20-25°C (68-77°F)

Inactive ingredients

cocoa butter, corn starch, methylparaben, propylparaben

Questions or comments?

Call weekdays 8 AM to 6 PM EST at
1-855-297-3031

Additional Information

Distributed by:

Haleon, Warren, NJ 07059

For most recent product information,

visit www.preparationh.com.

Trademarks are owned by or licensed

to the Haleon group of companies.

©2025 Haleon group of companies or its licensor.

Active ingredient made in Japan

Individually quality sealed for your protection.

Do Not Use if foil imprinted “PREPARATION H” is torn or damaged.

PRINCIPAL DISPLAY PANEL

HALEON

PREPARATION H
HEMORRHOIDAL
SUPPOSITORIES

Phenylephrine HCl 0.25%

Provides Relief from Multiple Symptoms

- Reduces Internal Hemorrhoidal Swelling
- Prompt Relief from Itching & Discomfort
- Also for Nighttime Relief

12 SUPPOSITORIES

216802 – Front Carton